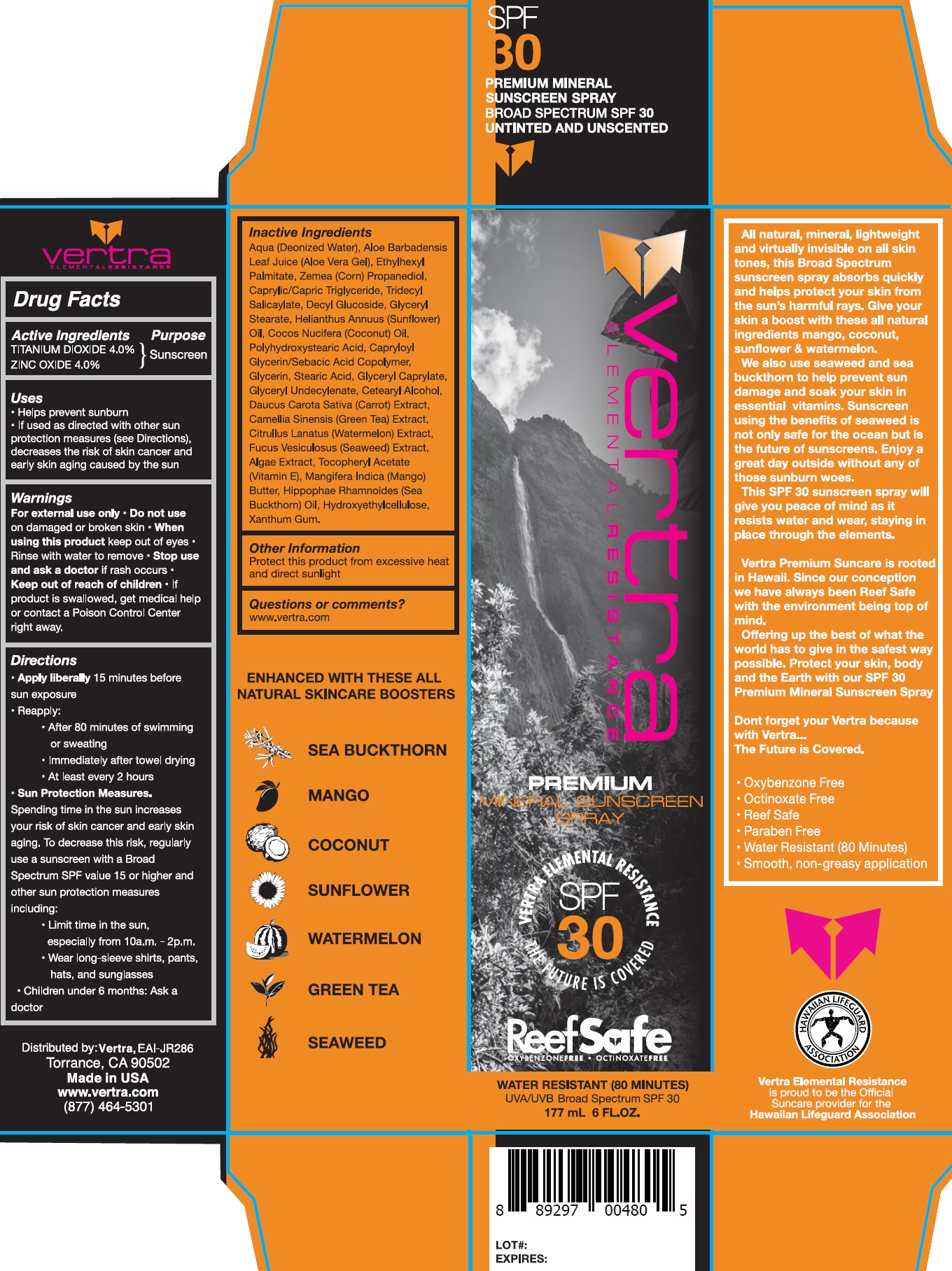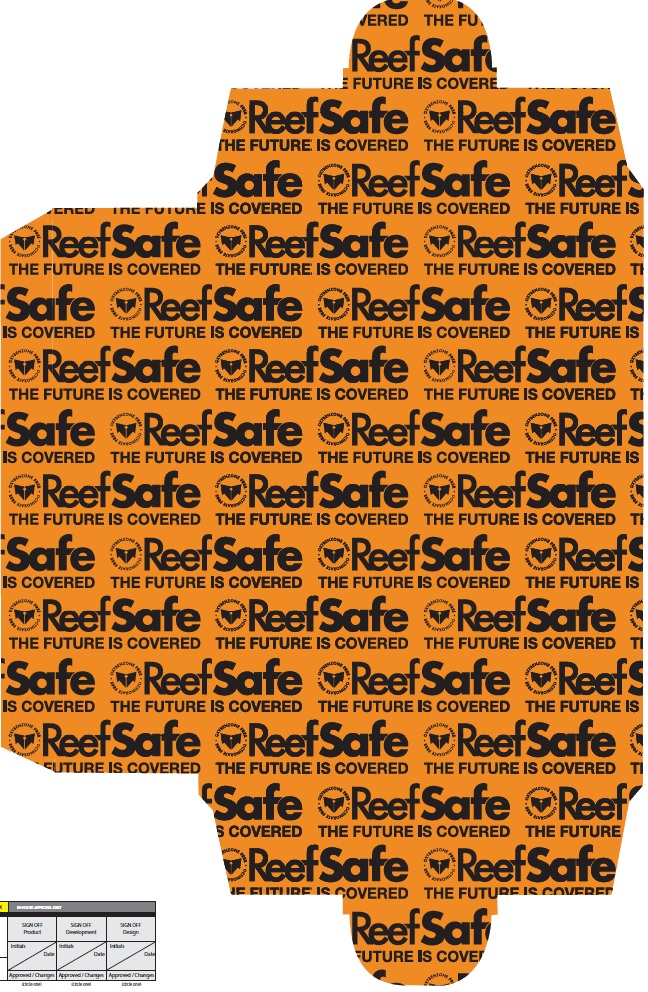 DRUG LABEL: VERTRA Premium Suncare SPF 30
NDC: 71014-029 | Form: SPRAY
Manufacturer: Eai-Jr286, Inc.
Category: otc | Type: HUMAN OTC DRUG LABEL
Date: 20231105

ACTIVE INGREDIENTS: TITANIUM DIOXIDE 40 mg/1 mL; ZINC OXIDE 40 mg/1 mL
INACTIVE INGREDIENTS: WATER; ALOE VERA LEAF; ETHYLHEXYL PALMITATE; CORN; PROPANEDIOL; MEDIUM-CHAIN TRIGLYCERIDES; TRIDECYL SALICYLATE; DECYL GLUCOSIDE; GLYCERYL MONOSTEARATE; COCONUT OIL; CAPRYLOYL GLYCERIN/SEBACIC ACID COPOLYMER (2000 MPA.S); GLYCERIN; STEARIC ACID; GLYCERYL CAPRYLATE; GLYCERYL 1-UNDECYLENATE; CETOSTEARYL ALCOHOL; CARROT; GREEN TEA LEAF; WATERMELON; NORI; MANGO; XANTHAN GUM

VERTRA Premium Suncare SPF 30 Spray

Active ingredient

Titanium Dioxide 5.0% Zinc Oxide 5.0%

Purpose

Sunscreen

Uses

• Helps prevent sunburn

• If used as directed with other sun protection measures (see Directions), decreases the risk of skin cancer and early skin aging caused by the sun

Warnings

For external use only

Do not use

- on damaged or broken skin

When using this product

• keep out of eyes

• Rinse with water to remove

Stop use and ask a doctor

if rash occurs

Keep out of reach of children

• If product is swallowed, get medical help or contact a Poison Control Center right away.

Directions

• Apply liberally 15 minutes before sun exposure

• Reapply:

• After 80 minutes of swimming or sweating

• Immediately after towel drying

• At least every 2 hours

• Spending time in the sun increases your risk of skin cancer and early skin aging. To decrease this risk, regularly use a sunscreen with a Broad Spectrum SPF value 15 or higher and other sun protection measures including: Sun Protection Measures.

• Limit time in the sun, especially from 10a.m. - 2p.m.

• Wear long-sleeve shirts, pants, hats, and sunglasses

• Children under 6 months: Ask a doctor

Inactive Ingredients

Aqua (Deonized Water), Aloe Barbadensis Leaf Juice (Aloe Vera Gel), Ethylhexyl Palmitate, Zemea (Corn) Propanediol, Caprylic/Capric Triglyceride, Tridecyl Salicaylate, Decyl Glucoside, Glyceryl Stearate, Helianthus Annuus (Sunflower) Oil, Cocos Nucifera (Coconut) Oil, Polyhydroxystearic Acid, Capryloyl Glycerin/Sebacic Acid Copolymer, Glycerin, Stearic Acid, Glyceryl Caprylate, Glyceryl Undecylenate, Cetearyl Alcohol, Daucus Carota Sativa (Carrot) Extract, Camellia Sinensis (Green Tea) Extract, Citrullus Lanatus (Watermelon) Extract, Fucus Vesiculosus (Seaweed) Extract, Algae Extract, Tocopheryl Acetate (Vitamin E), Mangifera Indica (Mango) Butter, Hippophae Rhamnoides (Sea Buckthorn) Oil, Hydroxyethylcellulose, Xanthum Gum.

Other Information

Protect this product from excessive heat and direct sunlight

Questions or comments?

www.vertra.com